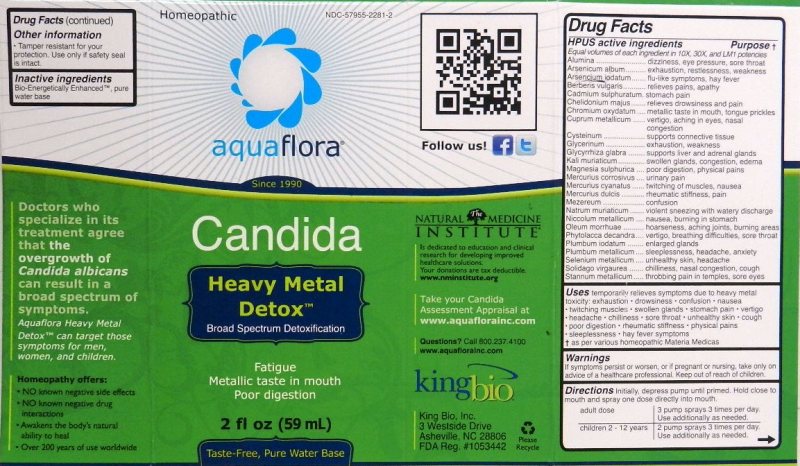 DRUG LABEL: Candida  Heavy Metal Detox
NDC: 57955-2281 | Form: LIQUID
Manufacturer: King Bio Inc.
Category: homeopathic | Type: HUMAN OTC DRUG LABEL
Date: 20111102

ACTIVE INGREDIENTS: ALUMINUM OXIDE 10 [hp_X]/59 mL; ARSENIC TRIOXIDE 10 [hp_X]/59 mL; ARSENIC TRIIODIDE 10 [hp_X]/59 mL; BERBERIS VULGARIS ROOT BARK 10 [hp_X]/59 mL; CADMIUM SULFIDE 10 [hp_X]/59 mL; CHELIDONIUM MAJUS 10 [hp_X]/59 mL; CHROMIC OXIDE 10 [hp_X]/59 mL; COPPER 10 [hp_X]/59 mL; CYSTEINE 10 [hp_X]/59 mL; GLYCERIN 10 [hp_X]/59 mL; GLYCYRRHIZA GLABRA 10 [hp_X]/59 mL; POTASSIUM CHLORIDE 10 [hp_X]/59 mL; MAGNESIUM SULFATE HEPTAHYDRATE 10 [hp_X]/59 mL; MERCURIC CHLORIDE 10 [hp_X]/59 mL; MERCURIC CYANIDE 10 [hp_X]/59 mL; CALOMEL 10 [hp_X]/59 mL; DAPHNE MEZEREUM BARK 10 [hp_X]/59 mL; SODIUM CHLORIDE 10 [hp_X]/59 mL; NICKEL 10 [hp_X]/59 mL; COD LIVER OIL 10 [hp_X]/59 mL; PHYTOLACCA AMERICANA ROOT 10 [hp_X]/59 mL; LEAD IODIDE 10 [hp_X]/59 mL; LEAD 10 [hp_X]/59 mL; SELENIUM 10 [hp_X]/59 mL; SOLIDAGO VIRGAUREA FLOWERING TOP 10 [hp_X]/59 mL; TIN 10 [hp_X]/59 mL
INACTIVE INGREDIENTS: WATER

Candida Heavy Metal Detox

Active Ingredients

HPUS active Ingredients

Equal volumes of each ingredient in 10X, 30X, and LM1 potencies.

Alumina

Arsenicum album

Arsenicum iodatum

Berberis vulgaris

Cadmium sulphuratum

Chelidonium majus

Chromium oxydatum

Cuprum metallicum

Cysteinum

Glycerinum

Glycyrrhiza glabra

Kali muriaticum

Magnesia sulphurica

Mercurius corrosivus

Mercurius cyanatus

mercurius dulcis

Mezereum

Natrum muriaticum

Niccolum metallicum

Oleum morrhuae

Phytolacca decandra

Plumbum iodatum

Plumbum metallicum

Selenium metallicum

Solidago virgaurea

Stannum metallicum

Reference image metal detox.jpg

Inactive Ingredient

Bio-Energetically Enhanced, pure water base.

Reference image metal detox.jpg

Dosage and Administration

Directions: Initially, depress pump until primed. Hold close to mouth and spray one dose directly into mouth.

Adult Dose 3 pump sprays 3 times per day. Use additionally as needed.

Children 2-12 years 2 pump sprays 3 times per day. Use additionally as needed.

Reference image metal detox.jpg

Purpose Section

HPUS active Ingredients Purpose

Alumina ..............................dizziness, eye pressure, sore throat

Arsenicum album.................exhaustion, restlessness, weakness

Arsenicum iodatum..............flu-like symptoms, hay fever

Berberis vulgaris..................relieves pains, apathy

Cadmium sulphuratum.........stomach pain

Chelidonium majus................relieves drowsiness and pain

Chromium oxydatum.............metallic taste in mouth, tongue prickles

Cuprum metallicum...............vertigo, aching in eyes, nasal congestion

Cysteinum............................supports connective tissue

Glycerinum...........................exhaustion, weakness

Glycyrrhiza glabra.................supports liver and adrenal glands

Kali muriaticum.....................swollen glands, congestion edema

Magnesia sulphurica.............poor digestion, physical pains

Mercurius corrosivus............urinary pain

Mercurius cyanatus..............twitching of muscles, nausea

mercurius dulcis...................rheumatic stiffness, pain

Mezereum............................confusion

Natrum muriaticum...............violent sneezing with watery discharge

Niccolum metallicum..............nausea, burning in stomach

Oleum morrhuae....................hoarseness, aching joints, burning areas

Phytolacca decandra..............vertigo, breathing difficulties sore throat

Plumbum iodatum...................enlarged glands

Plumbum metallicum...............sleeplessness, headache, anxiety

Selenium metallicum...............unhealthy skin, headache

Solidago virgaurea..................chilliness, nasal congestion, cough

Stannum metallicum................throbbing pain in temples, sore eyes

Reference image metal detox.jpg

Warnings

If symptoms persist or worsen, or if pregnant or nursing, take only on advice of a healthcare professional. Keep out of reach of children.

Other information

Tamper resistant for your protection. Use only if safety seal is intact.

Reference image metal detox.jpg

Keep Out Of Reach Of Children

Reference image metal detox.jpg

Indications and Usage

Uses temporarily relieves symptoms due to heavy metal toxicity:

- exhaustion
- drowsiness
- confusion
- nausea
- twitching muscles
- swollen glands
- stomach pain
- vertigo
- headache
- chilliness
- sore throat
- unhealthy skin
- cough
- poor digestion
- rheumatic stiffness
- physical pains
- sleeplessness
- hay fever symptoms

Reference image metal detox.jpg

PACKAGE LABEL

King Bio, Inc.

3 Westside Drive

Asheville, NC 28806

Reference image metal detox.jpg